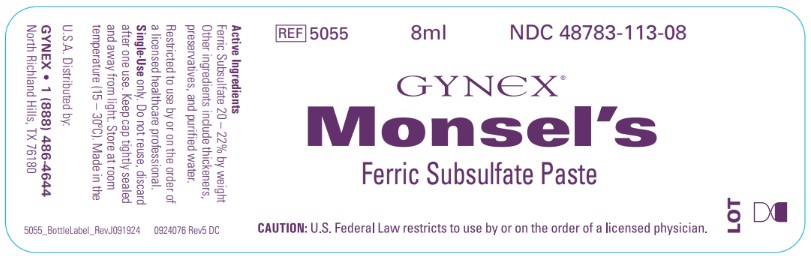 DRUG LABEL: Monsels Solution
NDC: 48783-113 | Form: PASTE
Manufacturer: Premier Dental Products Company
Category: prescription | Type: HUMAN PRESCRIPTION DRUG LABEL
Date: 20260113

ACTIVE INGREDIENTS: FERRIC SUBSULFATE 210 mg/1 g
INACTIVE INGREDIENTS: SILICON DIOXIDE; SODIUM BENZOATE; FERRIC SULFATE; WATER

Gynex Monsels

ACTIVE INGREDIENT

Ferric Subsulfate 20-22% by weight

INACTIVE INGREDIENT

Other Ingredients include thickeners, preservatives, and purified water

STORAGE AND HANDLING

Store at room temperature (15-30degC)

Keep cap tightly sealed

Protect from light

Mfg. for and distrib. by:

Gynex

North Richland Hills, TX

DOSAGE AND ADMINISTRATION

Do not reuse, discard after one use.

PACKAGE LABEL

NDC 48783-113-08

Gynex Monsel's Ferric Subsulfate Paste

REF 5055

Monsel's Ferric Subsulfate Paste 20-22%, Non-Sterile, Single-Patient Use

12 single applications - 8mL vials, 12 rayon-tipped applicators